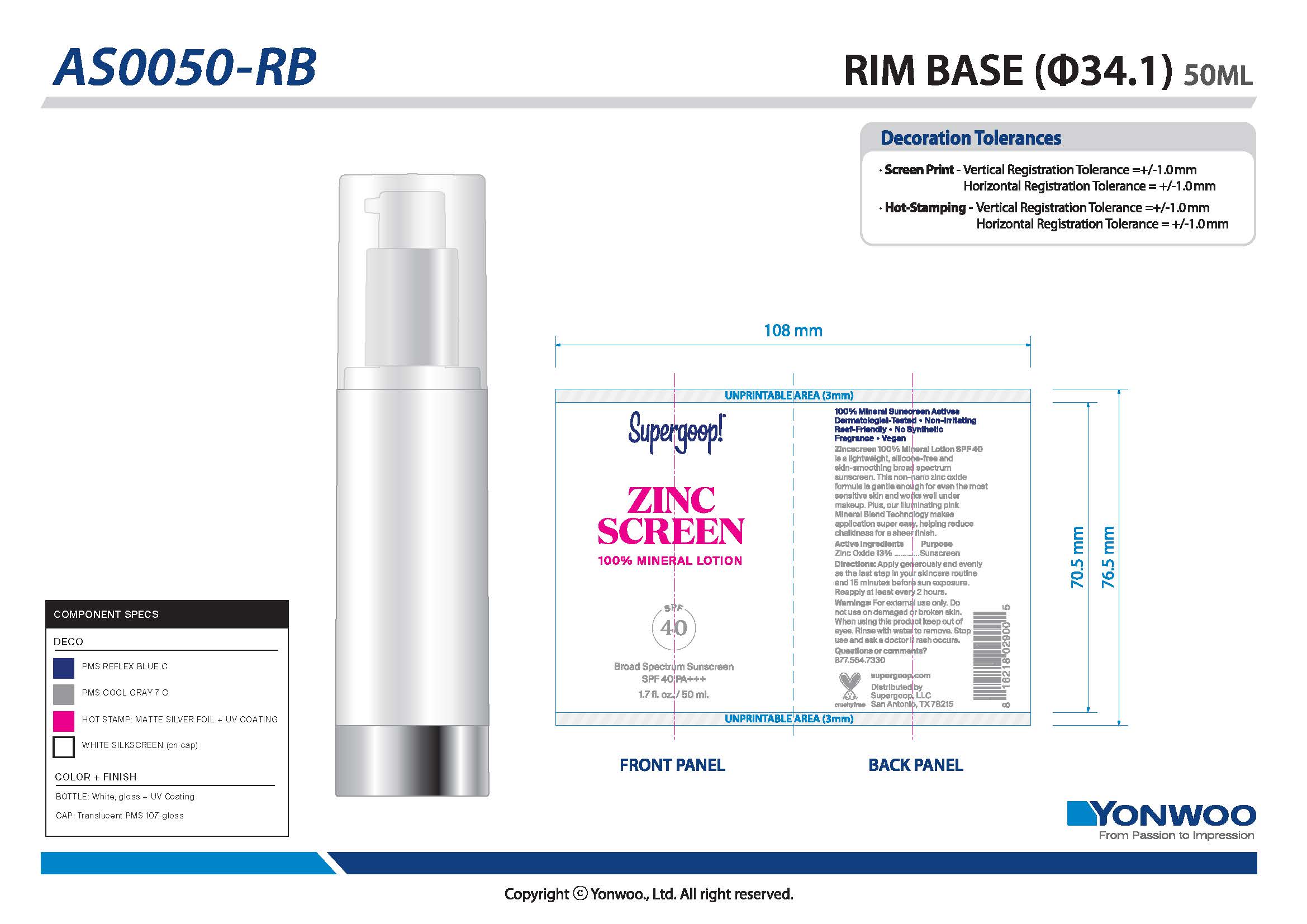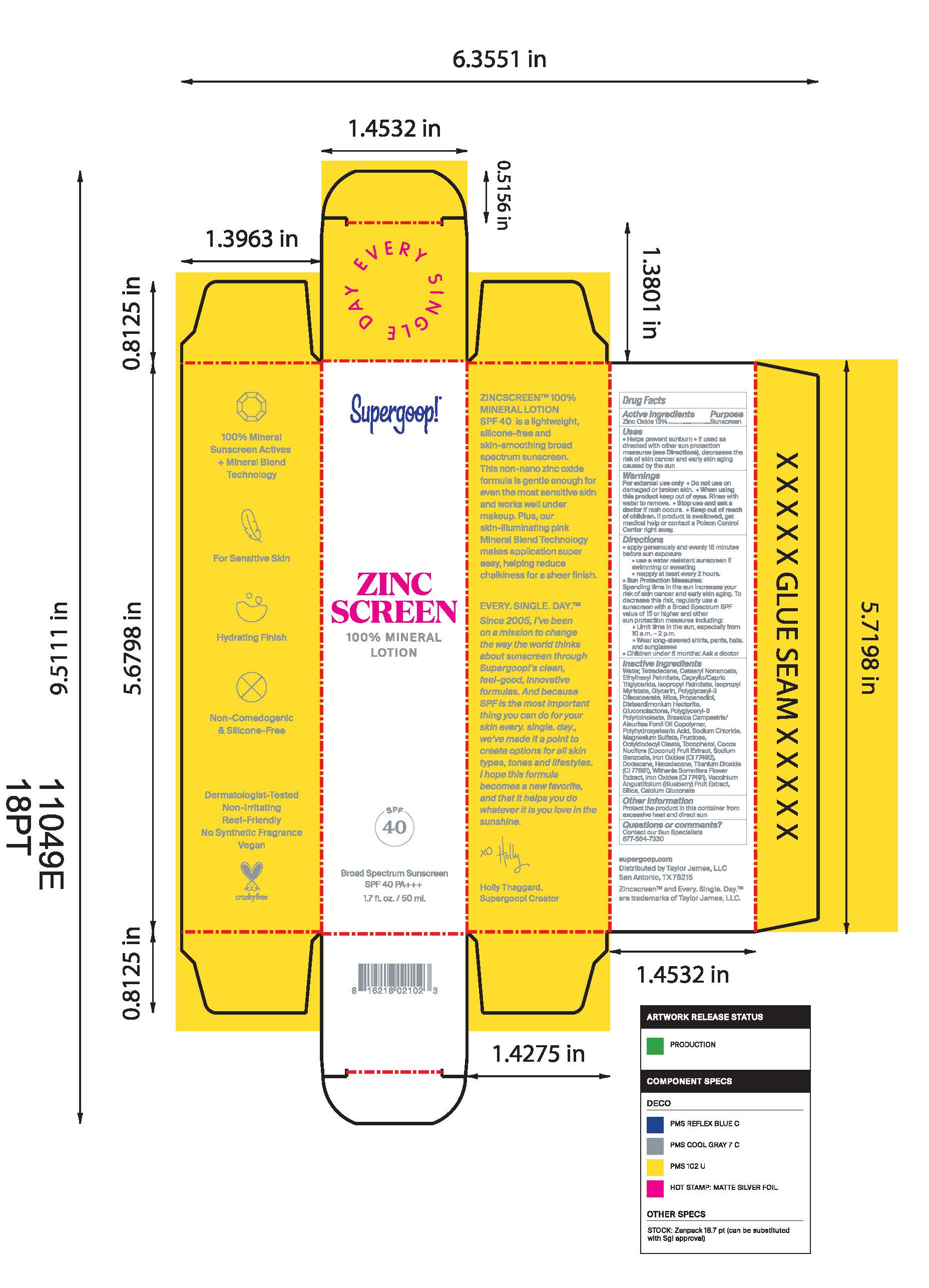 DRUG LABEL: Zinc Screen Broad Spectrum Sunscreen SPF 40
NDC: 75936-223 | Form: LOTION
Manufacturer: Supergoop, LLC
Category: otc | Type: HUMAN OTC DRUG LABEL
Date: 20241204

ACTIVE INGREDIENTS: ZINC OXIDE 13 g/100 mL
INACTIVE INGREDIENTS: GLUCONOLACTONE; POLYHYDROXYSTEARIC ACID (2300 MW); SODIUM CHLORIDE; SILICON DIOXIDE; PROPANEDIOL; OCTYLDODECYL OLEATE; CALCIUM GLUCONATE; ISOPROPYL PALMITATE; TETRADECANE; ETHYLHEXYL PALMITATE; MEDIUM-CHAIN TRIGLYCERIDES; ISOPROPYL MYRISTATE; FRUCTOSE; WATER; MAGNESIUM SULFATE ANHYDROUS; WITHANIA SOMNIFERA FLOWER; HEXADECANE; CETEARYL NONANOATE; MICA; TITANIUM DIOXIDE; TOCOPHEROL; GLYCERIN; COCONUT; SODIUM BENZOATE; FERRIC OXIDE YELLOW; DODECANE; FERRIC OXIDE RED; LOWBUSH BLUEBERRY; POLYGLYCERYL-3 DIISOSTEARATE; DISTEARDIMONIUM HECTORITE

Zinc Screen Broad Spectrum Sunscreen SPF 40

Active Ingredients Purpose

Zinc Oxide 13% Sunscreen

Uses

Helps prevent sunburn

If used as directed with other sun protection measures (see Directions), decreases the risk of skin cancer and early skin aging caused by the sun

Keep out of reach of children.

If product is swallowed, get medical help or contact a Poison Control Center right away.

Stop use and ask a doctor if rash occurs or irritation develops and lasts.

Warnings

Do not use on damaged or broken skin
When using this product keep out of eyes. Rinse with water to remove
For external use only

Directions

Apply generously and evenly 15 minutes before sun exposure
Use a water-resistant sunscreen if swimming or sweating
Reapply at least every 2 hours.
Sun Protection Measures Spending time in the sun increases your risk of
skin cancer and early skin aging. To decrease this risk, regularly use a
sunscreen with a Broad Spectrum SPF value of 15 or higher and other sun
protection measures including: • limit your time in the sun, especially from 10
a.m. – 2 p.m. • wear long-sleeved shirts, pants, hats, and sunglasses
Children under 6 months of age: ask a doctor.

Inactive Ingredients

Water, Tetradecane, Cetearyl Nonanoate, Ethylhexyl Palmitate, Caprylic/Capric Triglyceride, Isopropyl Myristate, Glycerin, Polyglyceryl-3 Diisostearate, Mica, Propanediol, Disteardimonium Hectorite, Gluconolactone, Polyglyceryl-6 Polyricinoleate, Brassica Campestris/Aleurites Fordi Oil Copolymer, Polyhydrostearic Acid, Sodium Chloride, Magnesium Sulfate, Fructose, Octyldodecyl Oleate, Tocopherol, Cocos Nucifera (Coconut) Fruit Extract, Sodium Benzoate, Iron oxides (CI 77492), Dodecane, Hexadecane, Titanium Dioxide (CI 77891), Withania Somnifera Flower Extract, Iron Oxides (CI 77491), Vaccinium Angustifolia (Blueberry) Fruit Extract, Silica, Calcium Gluconate

PACKAGE LABEL

Zinc Screen

100% Mineral Lotion

Broad Spectrum SPF 40 PA+++

1.7 fl. oz. / 50 ml.